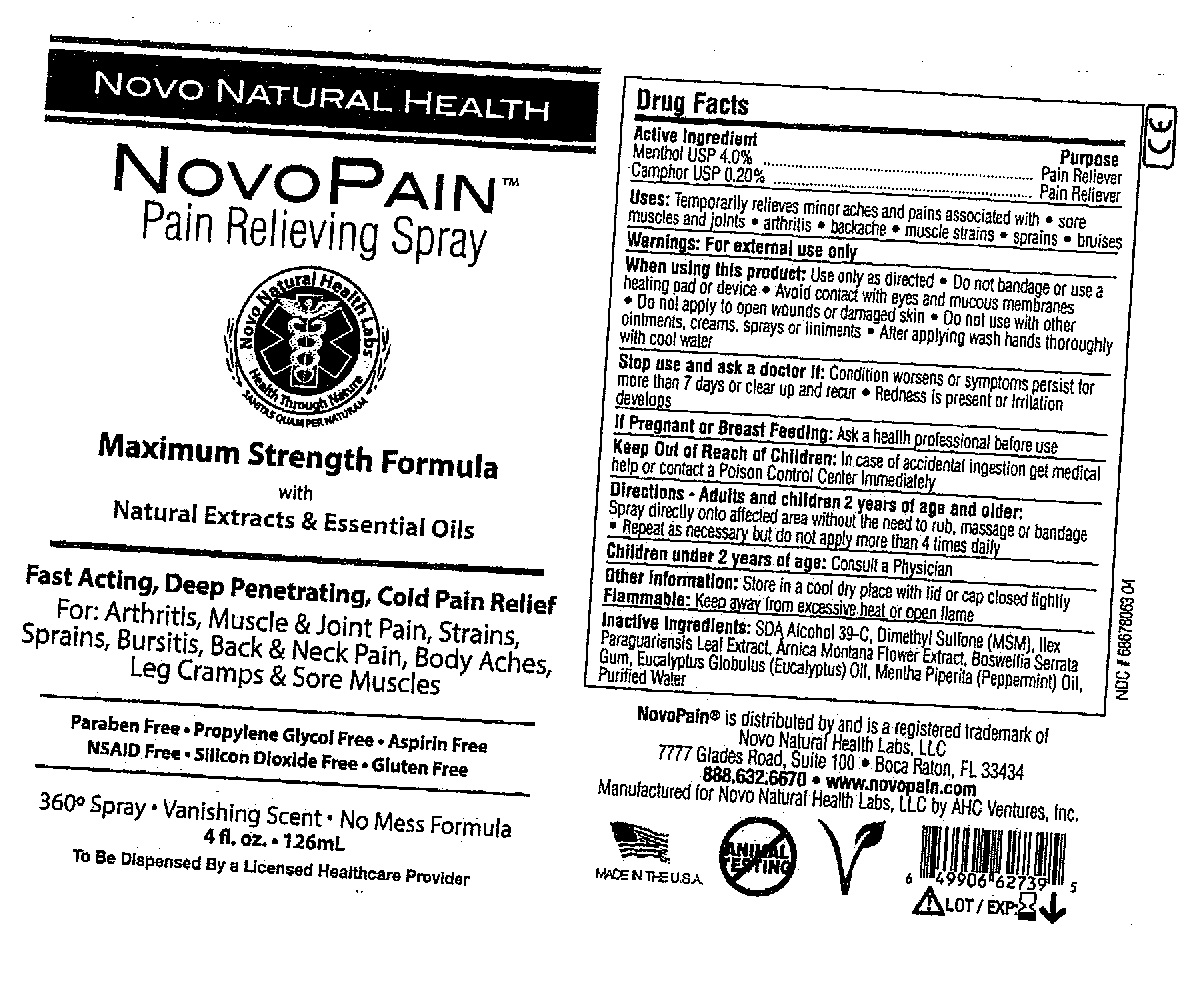 DRUG LABEL: NovoPain
NDC: 68678-063 | Form: SPRAY
Manufacturer: AHC VENTURES CORP
Category: otc | Type: HUMAN OTC DRUG LABEL
Date: 20151229

ACTIVE INGREDIENTS: MENTHOL 4 g/100 mL; CAMPHOR (SYNTHETIC) 0.2 g/100 mL
INACTIVE INGREDIENTS: ALCOHOL 51.4 mL/100 mL; DIMETHYL SULFONE 2 mL/100 mL; ILEX PARAGUARIENSIS LEAF 1 mL/100 mL; ARNICA MONTANA FLOWER 1 mL/100 mL; BOSWELLIA SERRATA WHOLE 1 mL/100 mL; EUCALYPTOL 0.05 mL/100 mL; WATER 39.3 mL/100 mL; PEPPERMINT OIL 0.05 mL/100 mL

Novopain Pain Relieving Spray

Uses

Temporarily releaves minor aches and pains associated with

- sore muscles and joints
- arthritis
- backache
- muscle strains
- sprains
- bruises

Inactive ingredients

SDA Alcohol 39-C, Dimethyl Sulfone (MSM), Ilex Paraguariensis Leaf Extract, Arnica Montana Flower Extract, Boswellia Serrata Gum, Eucalyptus Globulus (Eucalyptus) Oil, Mentha Piperita (Peppermint) Oil, Purified Water

Active Ingredients

Menthol USP 4.0%

Camphor USP .20%

Purpose

Pain Reliever

Warnings

For external use only
When using this product: Use only as directed

- Do not apply to open wonds or damaged skin
- Do not use with other ointments, creams, sprays or liniments
- After applying wash hands thoroughly with cool water

Stop use and ask a doctor if: Condition worsens or symptoms persists for more than 7 days or clear up and recur

- Redness is present or irritation develops

Keep Out Of Reach Of Children

In case of accidental ingestion get medical help or contact a Poison Control Center Immediately

Directions

Adults and children 2 years of age and older: Spray Directly onto affected area without the need to rub, massage, bandage

- Repeat as necessary

Other Information

Store in a cool dry place with lid or cap closed tightly

Flammable: Keep away from excessive heat or open flame

If Pregnant Or Breast Feeding

Ask a health professional before use.

Children under 2 Years of age:

Consult a physician

Novo Natural Health

NovoPain Pain Relieving Spray

Maximum Strength Formula with Natural Extracts & Essential Oils

Fast Acting, Deep Penetrating, Cold Pain Relief

For Arthritis, Muscle & Joint Pain, Strains, Sprains, Bursitis, Back & Neck Pain, Body Aches, Leg Cramps, & Sore Muscles

ParabenFree, Propylene Glycol Free, Asprin Free, NSAID Free, Silicon Dioxide Free, Gluten Free

360 Spray, Vanishing Scent, No Mess Formula

4 fl. oz, 126mL

To Be dispensed By a Licenced Healthcare Provider